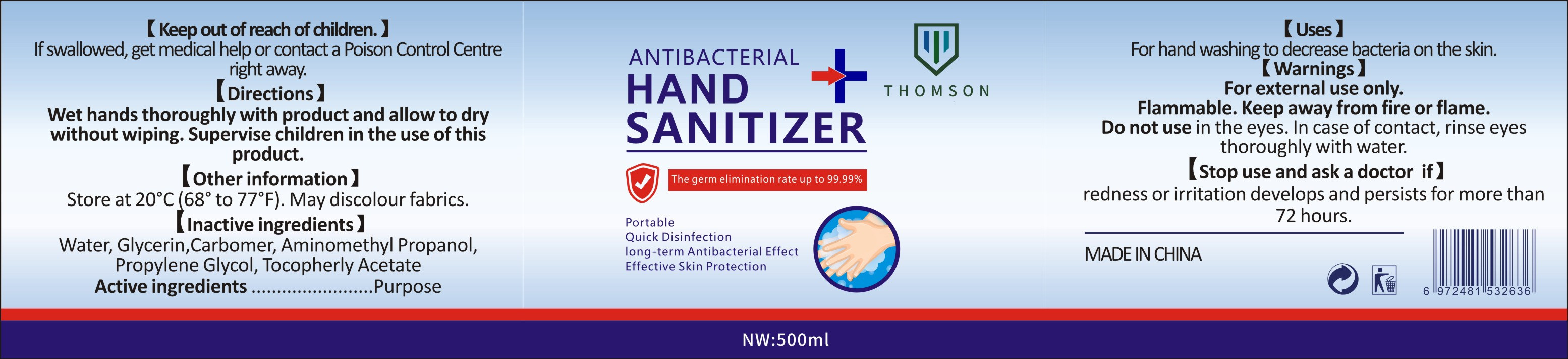 DRUG LABEL: Antibacterial Instant Hand Sanitizer
NDC: 55467-002 | Form: LIQUID
Manufacturer: INTENTLY (GUANGZHOU) BIOTECHNOLOGY CO., LTD.
Category: otc | Type: HUMAN OTC DRUG LABEL
Date: 20200603

ACTIVE INGREDIENTS: ALCOHOL 375 mL/500 mL
INACTIVE INGREDIENTS: TROLAMINE; WATER; CARBOMER HOMOPOLYMER, UNSPECIFIED TYPE

DOSAGE AND ADMINISTRATION

Store at 20°C (68° to 77°F),keep in dark place.

INACTIVE INGREDIENT

Water、Carbomer、Triethanolamine

INDICATIONS AND USAGE

Wet hands thoroughly with product and allow to dry without wiping. Supervise children in the use of this product.

ACTIVE INGREDIENT

Ethanol

keep out of reach of children

PURPOSE

Disinfection
Sterilization

WARNINGS

For external use only.Flammable. Keep away from fire or flame.Do not use in the eyes. In case of contact,rinse eyes thoroughly with water.